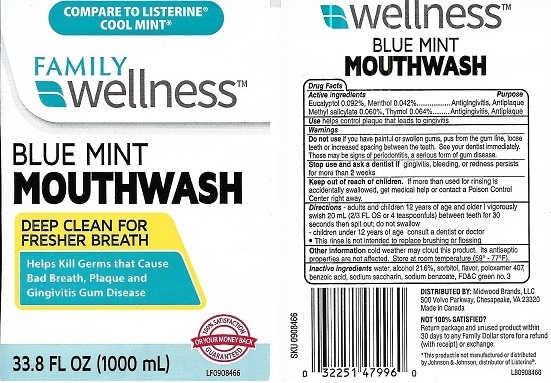 DRUG LABEL: Family Wellness
NDC: 55319-230 | Form: MOUTHWASH
Manufacturer: Family Dollar Services Inc.
Category: otc | Type: HUMAN OTC DRUG LABEL
Date: 20210823

ACTIVE INGREDIENTS: EUCALYPTOL 0.092 g/100 mL; MENTHOL 0.042 g/100 mL; METHYL SALICYLATE 0.06 g/100 mL; THYMOL 0.064 g/100 mL
INACTIVE INGREDIENTS: WATER; ALCOHOL; SORBITOL; POLOXAMER 407; BENZOIC ACID; SACCHARIN SODIUM; SODIUM BENZOATE; FD&C GREEN NO. 3

Family Wellness Blue Mint Mouthwash

Drug Facts

Active ingredients
Eucalyptol 0.092%, Menthol 0.042%

Methyl Salicylate 0.060%, Thymol 0.064%

Purpose

Antigingivitis, Antiplaque

Antigingivitis, Antiplaque

INDICATIONS AND USAGE

Usehelps control plaque that leads to gingivitis

Warnings

Do not use if you have painful or swollen gums, pus from the gum line, loose teeth or increased spacing between the teeth. See your dentist immediately. These may be signs of periodontitis, a serious form of gum disease.

Stop use and ask a dentist if gingivitis, bleeding or redness persists for more than 2 weeks

Keep out of reach of children. If more than used for rinsing is accidentally swallowed, get medical help or contact a Poison Control Center right away.

Directions

– adults and children 12 years of age and older: vigorously swish 20 mL (2/3 FL OS or 4 teaspoonfuls) between teeth for 30 seconds then spit out; do not swallow

– children under 12 years of age - consult a dentist or doctor

• This rinse is not intended to replace brushing or flossing

Other information cold weather may cloud this product. Its antiseptic properties are not affected . Store at room temperature (59° - 77°F)

INACTIVE INGREDIENT

Inactive Ingredients water, alcohol 21.6%, sorbitol, flavor, poloxamer 407, benzoic acid, sodium saccharin, sodium benzoate, FD&C green no.3

DISTRIBUTED BY: Midwood Brands, LLC

500 Volvo Parkway, Chesapeake, VA 23320

Made in Canada

* This product is not manufactured or distributed by Johnson & Johnson, distributor of Listerine®.

PACKAGE LABEL

COMPARE TO LISTERINE® COOL MINT*

FAMILY wellness™

BLUE MINT

MOUTHWASH

DEEP CLEAN FOR FRESHER BREATH

Helps Kill Germs that Cause Bad Breath, Plaque and Gingivitis Gum Disease

33.8 FL OZ (1000 mL)